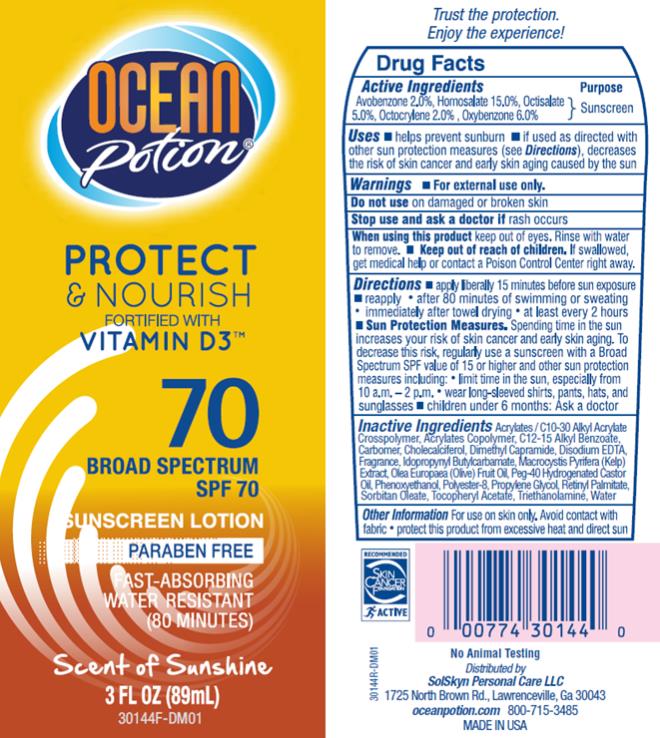 DRUG LABEL: OP SPF 70 Anti Aging Sunscreen
NDC: 70281-221 | Form: LOTION
Manufacturer: SolSkyn Personal Care LLC
Category: otc | Type: HUMAN OTC DRUG LABEL
Date: 20180215

ACTIVE INGREDIENTS: AVOBENZONE 2 g/100 g; HOMOSALATE 15 g/100 g; OCTOCRYLENE 2 g/100 g; OCTISALATE 5 g/100 g; OXYBENZONE 6 g/100 g
INACTIVE INGREDIENTS: CARBOMER INTERPOLYMER TYPE A (55000 CPS); ALKYL (C12-15) BENZOATE; CARBOXYPOLYMETHYLENE; CHOLECALCIFEROL; DIMETHYL CAPRAMIDE; EDETATE DISODIUM ANHYDROUS; IODOPROPYNYL BUTYLCARBAMATE; MACROCYSTIS PYRIFERA; OLIVE OIL; POLYOXYL 40 HYDROGENATED CASTOR OIL; PHENOXYETHANOL; POLYESTER-8 (1400 MW, CYANODIPHENYLPROPENOYL CAPPED); PROPYLENE GLYCOL; VITAMIN A PALMITATE; SORBITAN MONOOLEATE; ALPHA-TOCOPHEROL ACETATE; TROLAMINE; WATER

OP Protect Nourish Sunscreen Ltn SPF 70 3oz

OP SPF 70 Anti Aging Sunscreen

Active ingredients

Avobenzone 2.0%

Active ingredients

Homosalate 15.0%

Active ingredients

Octisalate 5.0%

Active ingredients

Octocrylene 2.0%

Active ingredients

Oxybenzone 6.0%

Purpose

Sunscreen

Uses

• Helps prevent sunburn.

• If used as directed with other sun protection measures (see Directions), decreases the risk of skin cancer and early skin aging caused by the sun.

Warnings

• For external use only.

• Keep out of reach of children.

If swallowed, get medical help or contact a Poison Control Center right away.

Directions

• Apply liberally 15 minutes before sun exposure.

• Re-apply:

• after 80 minutes of swimming or sweating

• immediately after towel drying

• at least every 2 hours

• Sun Protection Measures. Spending time in the sun increases your risk of skin cancer and early skin aging. To decrease this risk, regularly use a sunscreen with a Broad Spectrum SPF value of 15 or higher and other sun protection measures including:

• limit time in the sun, especially from 10 a.m.-2 p.m.

• wear long-sleeved shirts, pants, hats and sunglasses

• Children under 6 months: ask a doctor.

Inactive Ingredients

Acrylates / C10-30 Alkyl Acrylate Crosspolymer, Acrylates Copolymer, C12-15 Alkyl Benzoate, Carbomer, Cholecalciferol, Dimethyl Capramide, Disodium EDTA, Fragrance, Iodopropynyl Butylcarbamate, Macrocystis Pyrifera (Kelp) Extract, Olea Europaea (Olive) Fruit Oil, Peg-40 Hydrogenated Castor Oil, Phenoxyethanol, Polyester-8, Propylene Glycol, Retinyl Palmitate, Sorbitan Oleate, Tocopheryl Acetate, Triethanolamine, Water

Other Information

• For use on skin only. Avoid contact with fabric.

• Protect this product from excessive heat and direct sun.

PRINCIPAL DISPLAY PANEL

Ocean Potion
Protect
& Nourish
Vitamin D3
SPF 70
3 fl oz (89 mL)